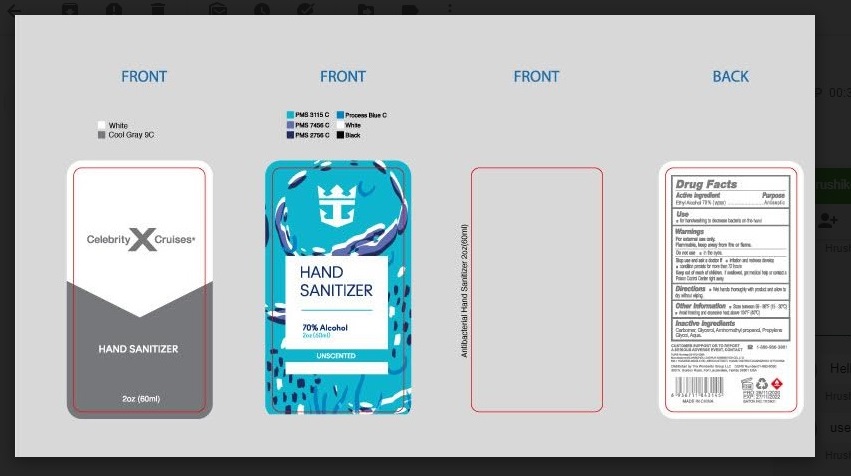 DRUG LABEL: Anti-Bacterial Hand Sanitizer
NDC: 77027-112 | Form: GEL
Manufacturer: GUANGZHOU ZUOFUN COSMETICS CO., LTD.
Category: otc | Type: HUMAN OTC DRUG LABEL
Date: 20210105

ACTIVE INGREDIENTS: ALCOHOL 75 mL/100 mL
INACTIVE INGREDIENTS: WATER; PROPYLENE GLYCOL; GLYCERIN; CARBOMER HOMOPOLYMER, UNSPECIFIED TYPE; AMINOMETHYLPROPANOL

Anti-Bacterial Hand Sanitizer

Active Ingredients

ETHYL ALCOHOL 75%

Purpose

Antiseptic

Uses

- FOR HANDWASHING TO DECREASE BACTERIA ON THE HAND

Warnings

- FOR EXTERNAL USE ONLY. FLAMMABLE, KEEP AWAY FROM FIRE OR FLAME
- DO NOT USE IN THE EYES

STOP USE AND ASK A DOCTOR IF:

- IRRITATION AND REDNESS DEVELOP
- CONDITION PERSISTS FOR MORE THAN 72 HOURS

KEEP OUT OF REACH OF CHILDREN.

- IF SWALLOWED, GET MEDICAL HELP OR CONTACT POISON CONTROL CENTER RIGHT AWAY

Directions

WET HANDS THOROUGHLY WITH PRODUCT AND ALLOW TO DRY WITHOUT WIPING.

Other Information

CUSTOMER SUPPORT OR TO REPORT A SERIOUS ADVERSE EVENT, CONTACT 1-888-986-3861

Inactive ingredients

AQUA, PROPYLENE GLYCOL, GLYCEROL, CARBOMER, AMINOMETHYL PROPANOL